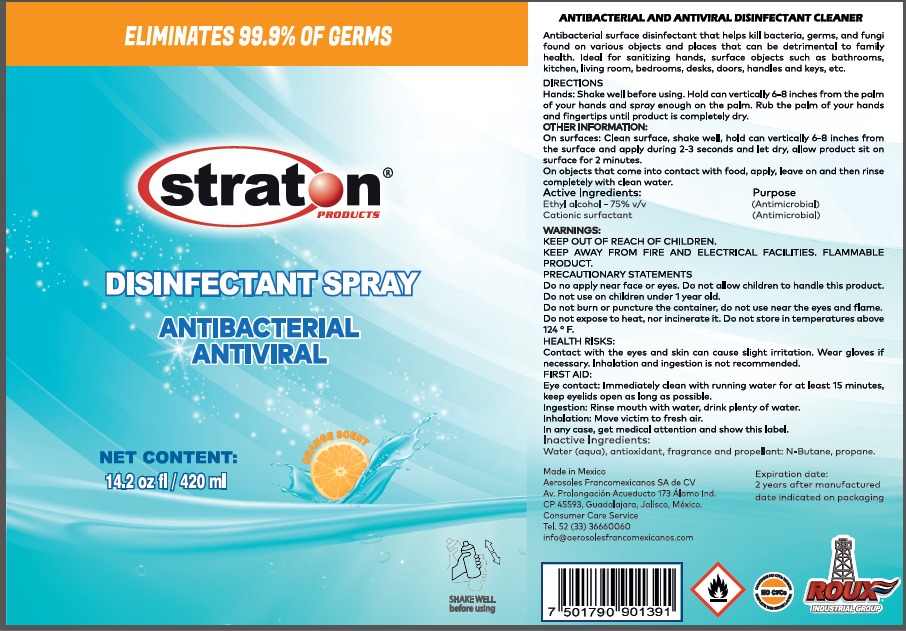 DRUG LABEL: STRATON
NDC: 80105-1000 | Form: AEROSOL
Manufacturer: Aerosoles Francomexicanos, S.A. de C.V.
Category: otc | Type: HUMAN OTC DRUG LABEL
Date: 20220128

ACTIVE INGREDIENTS: ALCOHOL 0.4643 mL/1 mL; N-ALKYL ETHYLBENZYL DIMETHYL AMMONIUM CHLORIDE (C12-C14) 0.0006 mg/1 mL
INACTIVE INGREDIENTS: BUTANE 0.2857 mL/1 mL; SODIUM NITRATE N-15 0.0019 mL/1 mL; WATER 0.1513 mL/1 mL; PROPANE 0.0952 mL/1 mL

STRATON DISINFECTANT SPRAY

ACTIVE INGREDIENTS

ETHYL ALCOHOL

CATIONIC SURFACTANT

INACTIVE INGREDIENTS

WATER, ANTIOXIDANT, FRAGRANCE, AND PROPELLANT: N-BUTANE, PROPANE

INDICATIONS AND USAGE

HANDS; SHAKE WELL BEFORE USING.

HOLD CAN VERTICALLY 6 - 8 INCHES FROM THE PALM OF YOUR HANDS AND SPRAY ENOUGH ON THE PALM.

RUB THE PALM OF YOUR HANDS AND FINGERTIPS UNTIL PRODUCT IS COMPLETELY DRY.

DOSAGE AND ADMINISTRATION

SPRAY ENOUGH PRODUCT ON THE PALM TO RUB YOUR HANDS AND FINGERTIPS UNTIL PRODUCT IS COMPLETELY DRY.

WARNINGS AND PRECAUTIONS

DO NOT APPLY NEAR FACE OR EYES

DO NOT ALLOW CHILDREN TO HANDLE THE PRODUCT

DO NOT USE ON CHILDREN UNDER 1 YEAR OLD.

DO NOT BURN OR PUNCTURE THE CONTAINER,

DO NOT USE NEAR THE EYES AND FLAME.

DO NOT EXPOSE TO HEAT, NOR INCINERATE IT.

DO NOT STORE IN TEMPERATURES ABOVE 124° F.

WARNINGS

FLAMMABLE PRODUCT

KEEP OUT OF REACH OF CHILDREN

PURPOSE

ANTIMICROBIAL

DO NOT USE ON CHILDREN UNDER 1 YEAR OLD.

ASK A DOCTOR SECTION

EYE CONTACT

INGESTION

INHALATION

IN ANY CASE GET MEDICAL ATTENTION AND SHOW THIS LABEL